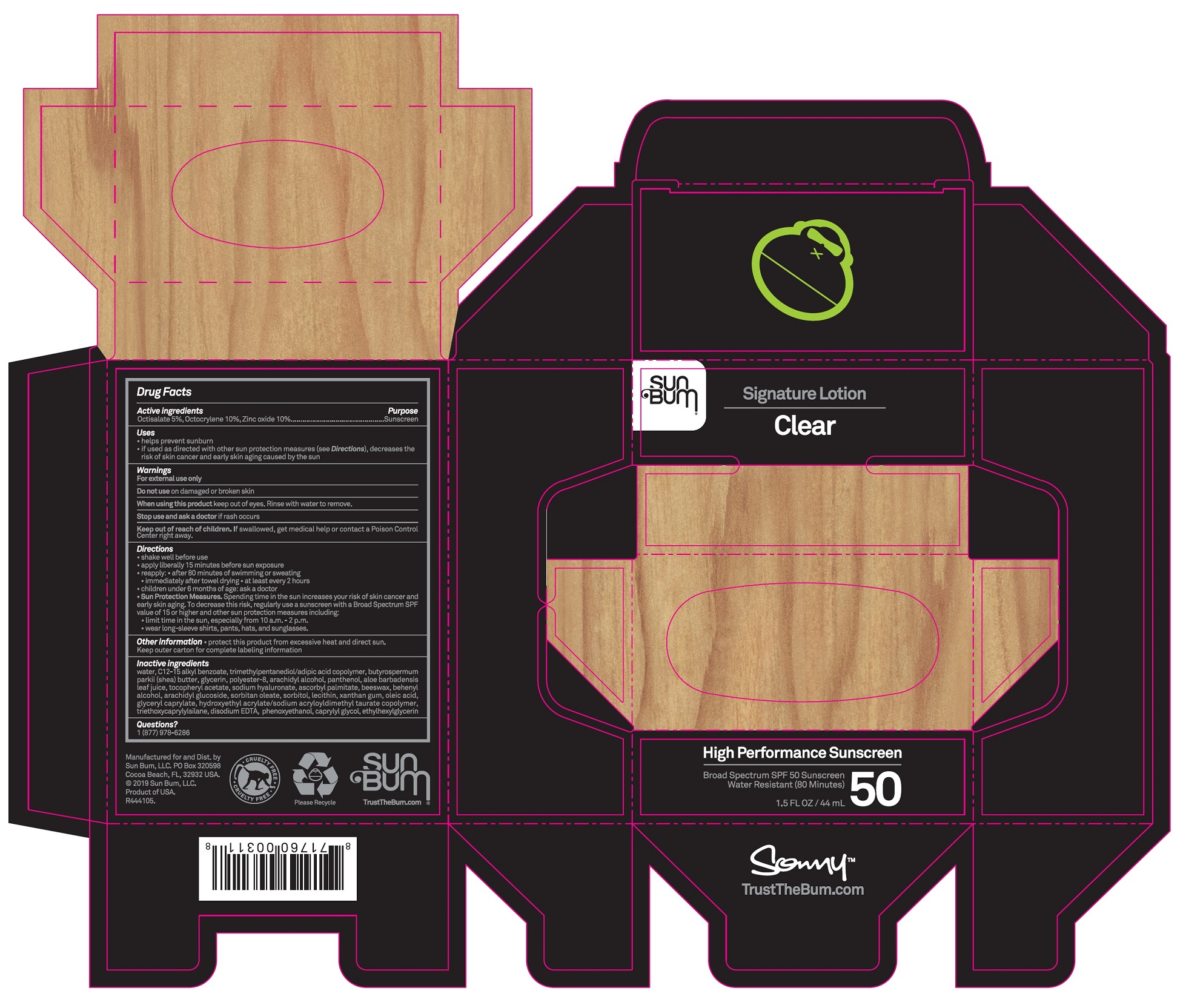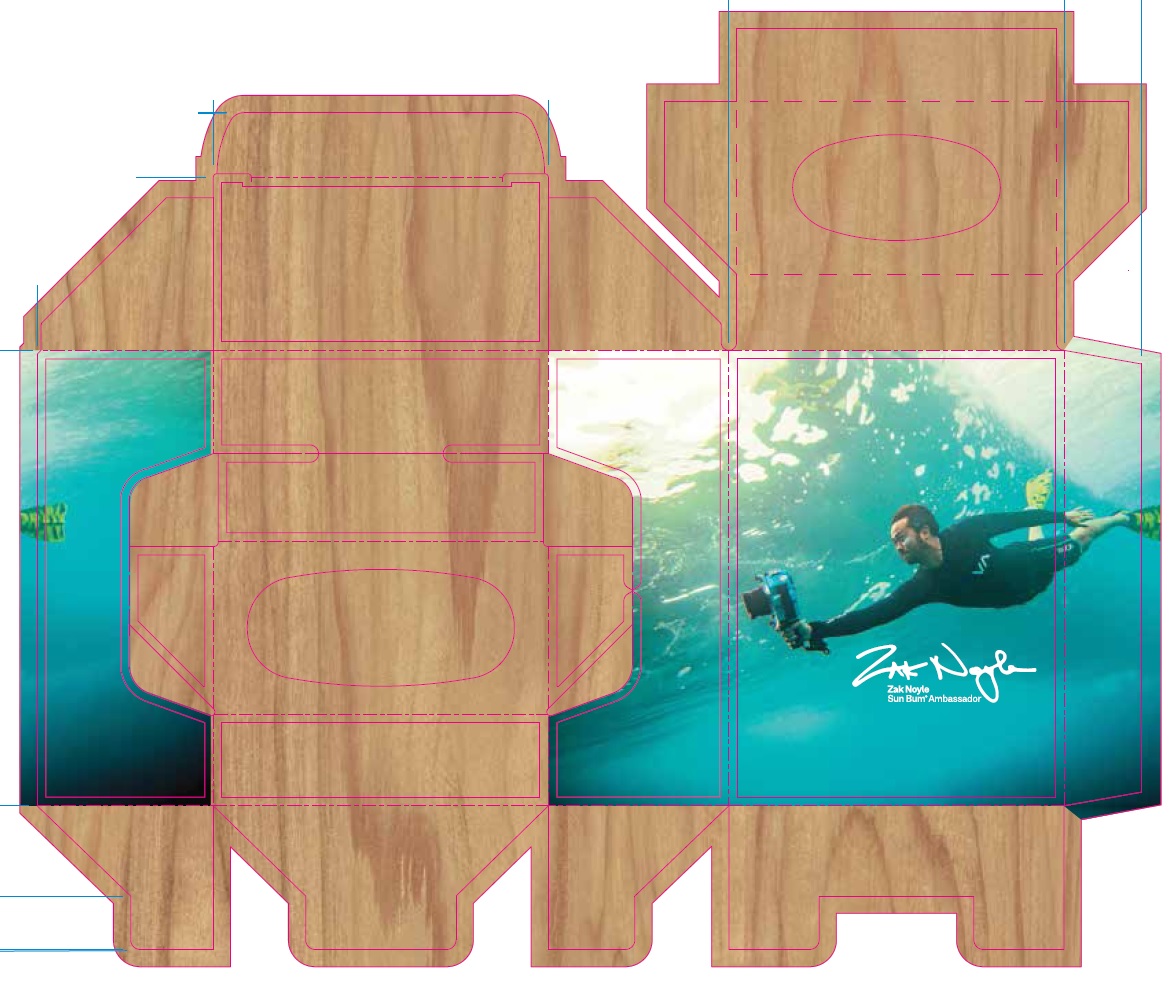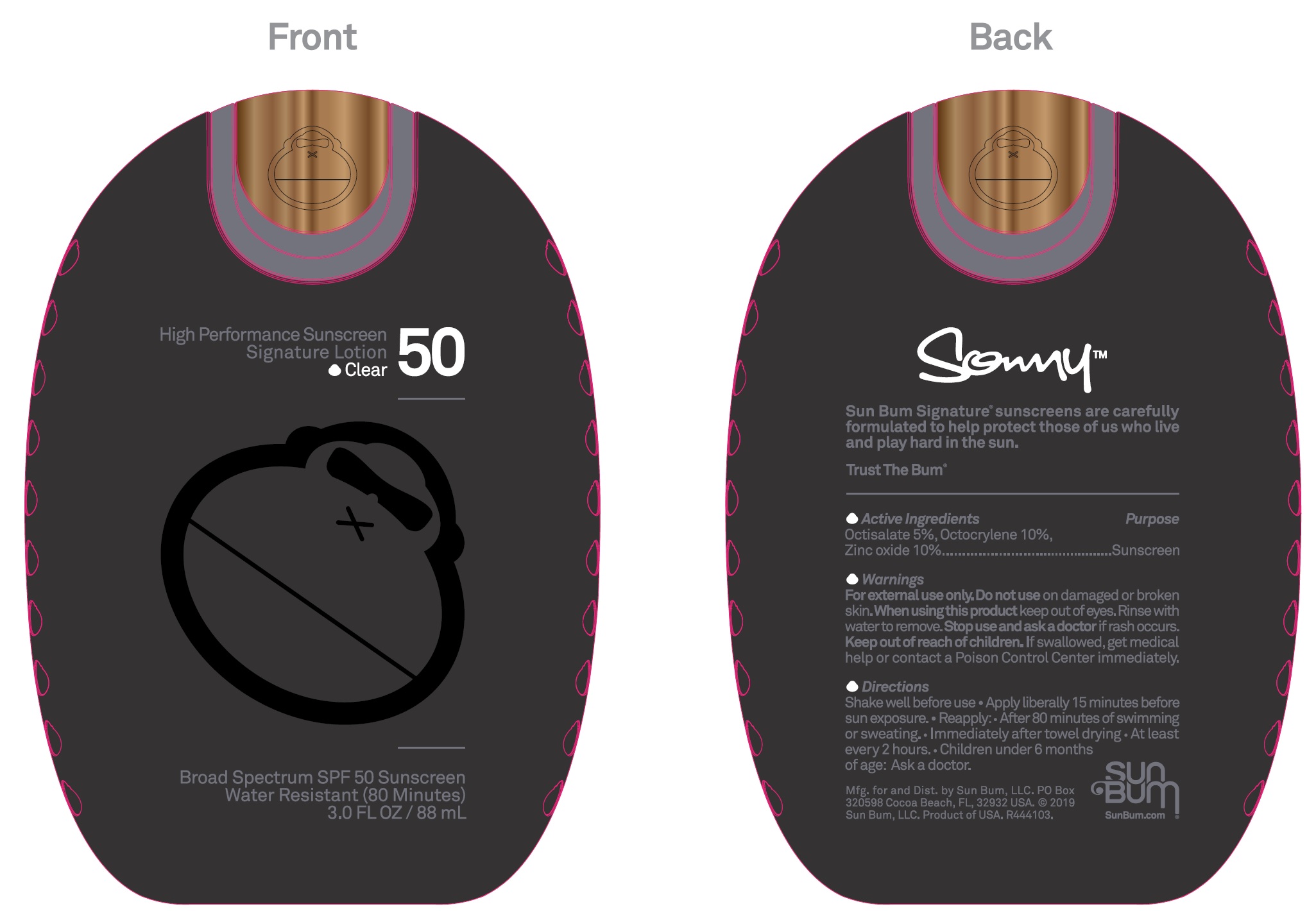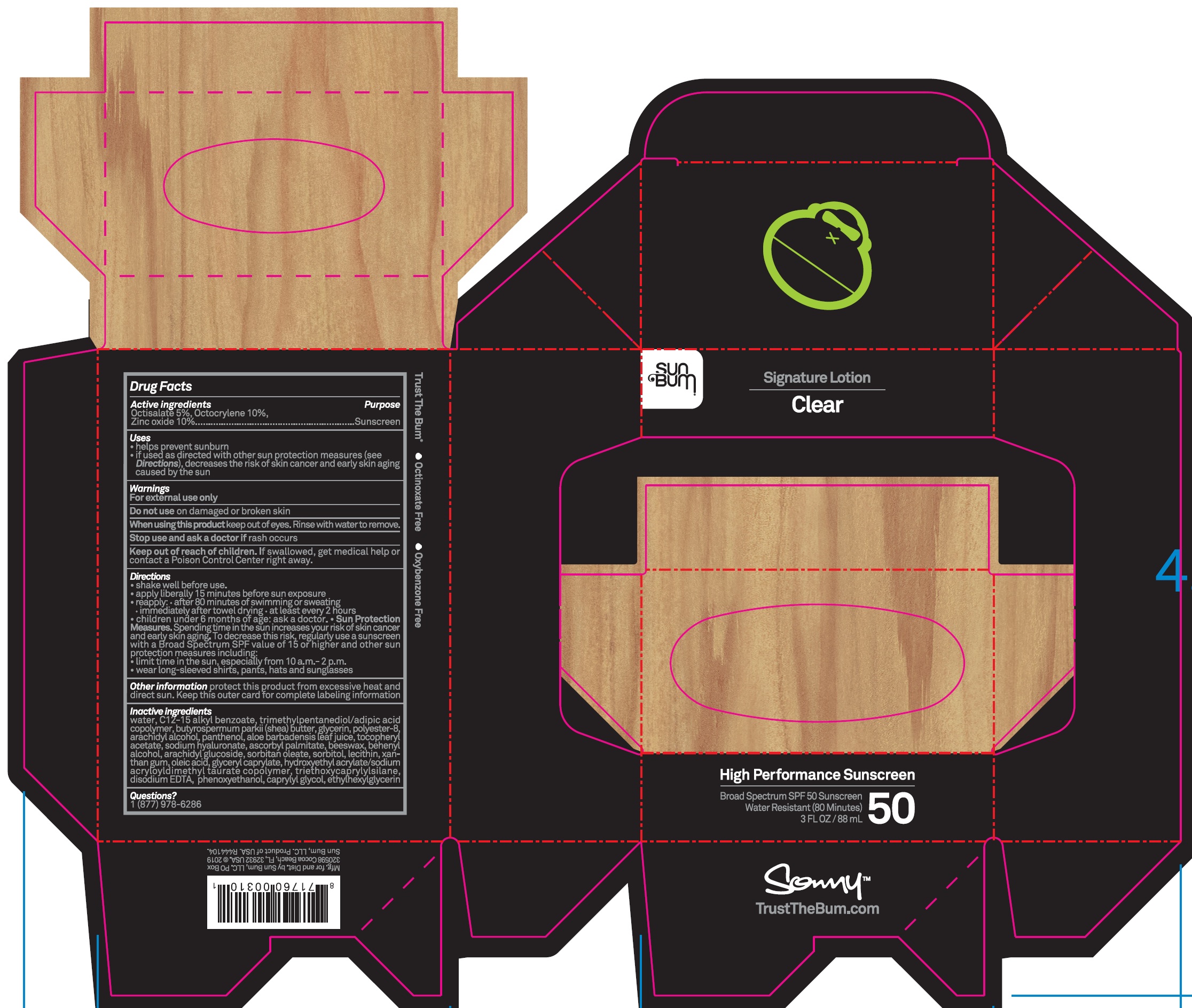 DRUG LABEL: Sun Bum Signature Clear SPF 50
NDC: 69039-617 | Form: LOTION
Manufacturer: Sun Bum LLC
Category: otc | Type: HUMAN OTC DRUG LABEL
Date: 20220204

ACTIVE INGREDIENTS: OCTISALATE 50 mg/1 mL; OCTOCRYLENE 100 mg/1 mL; ZINC OXIDE 100 mg/1 mL
INACTIVE INGREDIENTS: WATER; ALKYL (C12-15) BENZOATE; GLYCERIN; ARACHIDYL ALCOHOL; PANTHENOL; ALOE VERA LEAF; .ALPHA.-TOCOPHEROL ACETATE; HYALURONATE SODIUM; ASCORBYL PALMITATE; YELLOW WAX; DOCOSANOL; ARACHIDYL GLUCOSIDE; SORBITAN MONOOLEATE; SORBITOL; XANTHAN GUM; OLEIC ACID; GLYCERYL CAPRYLATE; EDETATE DISODIUM ANHYDROUS; PHENOXYETHANOL; CAPRYLYL GLYCOL; ETHYLHEXYLGLYCERIN

Sun Bum Signature Lotion Clear SPF 50

Active ingredients

Octisalate 5%, Octocrylene 10%. Zinc oxide 10%

Purpose

Sunscreen

Uses

- helps prevent sunburn
- if used as directed with other sun protection measures (see Directions), decreases the risk of skin cancer and early skin aging caused by the sun

Warnings

For externel use only

Do not use

on damaged or broken skin

When using this product

keep out of eyes. Rinse with water to remove.

Stop use and ask a doctor

if rash occurs

Keep out of reach of children.

If swallowed, get medical help or contact a Poison Control Center right away.

Directions

- shake well before use
- apply liberally 15 minutes before sun exposure
- reapply:
- after 80 minutes of swimming or sweating
- immediately after towel drying
- at least every 2 hours
- children under 6 months of age:ask a doctor
- Sun Protection Measures. Spending time in the sun increases your risk of skin cancer and early skin aging. To decrease this risk, regularly use a sunscreen with a Broad Spectrum SPF value of 15 or higher and other sun protection measures including:
- limit time in the sun, especially from 10a.m. - 2.p.m.
- wear long-sleeve shirts, pants, hats, and sunglasses.

Other information

- protect this product from excessive heat and direct sun. Keep outer carton for complete labeling information

Inactive ingredients

water, C12-15 alkyl benzoate, triethylpentanediol/ adipic acid copolymer, butyrospermum parkii (shee) butter, glycerin, polyster-8, arachidyl alcohol, panthenol, aloe barbadensis leaf juice, tocopheryl acetate, sodium hyaluronate, ascorbyl palmitate, beeswax, behenylalcohol, arachidyl glucoside, sorbitan oleate, sorbitol, lecithin, xanthan gum, oleic acid, glyceryl caprylate, hydroxyethyl acrylate/sodium acryloyldimethyl taurate copolymer, triethoxycaprylylate, disodium EDTA, phenoxyethanol, caprylyl glycol, ethylhexylglycerin

Questions?

1(877)978-6286